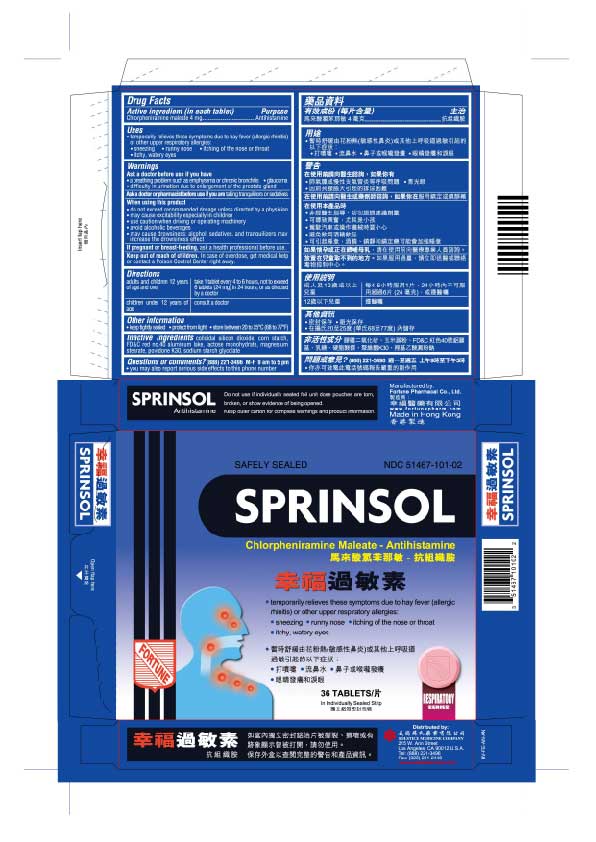 DRUG LABEL: SPRINSOL
NDC: 51467-101 | Form: TABLET
Manufacturer: FORTUNE PHARMACAL COMPANY LIMITED
Category: otc | Type: HUMAN OTC DRUG LABEL
Date: 20251113

ACTIVE INGREDIENTS: CHLORPHENIRAMINE MALEATE 4 mg/1 1
INACTIVE INGREDIENTS: SILICON DIOXIDE; STARCH, CORN; FD&C RED NO. 40; LACTOSE MONOHYDRATE; MAGNESIUM STEARATE; POVIDONE K30; SODIUM STARCH GLYCOLATE TYPE A POTATO

DRUG FACTS

Active ingredients (in each tablet)
Chlorpheniramine maleate 4 mg

Purpose
Antihistamine

Uses
temporarily relieves these symptoms due to hay fever (allergic rhinitis) or other upper respiratory allergies:
sneezing
runny nose
itching of the nose or throat
itchy, watery eyes

Warnings
Ask a doctor before use if you have
a breathing problem such as emphysema or chronic bronchitis
glaucoma
difficulty in urination due to enlargement of the prostate gland

Ask a doctor or pharmacist before use if you are
taking sedatives or tranquilizers

When using this product
do not exceed recommended dosage unless directed by a physician
may cause excitability especially in children
use caution when driving or operating machinery
avoid alcoholic beverages
may cause drowsiness; alcohol, sedatives, and tranquilizers may increase the drowsiness effect

PREGNANCY OR BREAST FEEDING

If pregnant or breast-feeding, ask a health professional before use.

Keep out of reach of children. In case of overdose, get medical help or contact a Poison Control Center right away

Directions
adults and children 12 years of age and over: take 1 tablet every 4 to 6 hours, not to exceed 6 tablets (24 mg) in 24 hours, or as directed by a doctor
children under 12 years of age: consult a doctor

Other information
keep tightly sealed
protect from light
store between 20 to 25 C (68 to 77 F)

Inactive ingredients
colloidal silicon dioxide, corn starch, FD C red no. 40 aluminum lake, lactose monohydrate, magnesium stearate, povidone K30, sodium starch glycolate

Questions or comments? (888) 221-3496 M-F 9 am to 5 pm
you may also report serious side effects to this phone number

PACKAGE LABEL

Sprinsol

Safely Sealed

NDC 51467-101-02

Chlorpheniramine maleate - Antihistamine

temporarily relieves these symptoms due to hay fever (allergic rhinitis) or other upper respiratory allergies:
sneezing
runny nose
itching of the nose or throat
itchy, watery eyes

36 Tablets

In Individually Sealed Strip

Respiratory Series